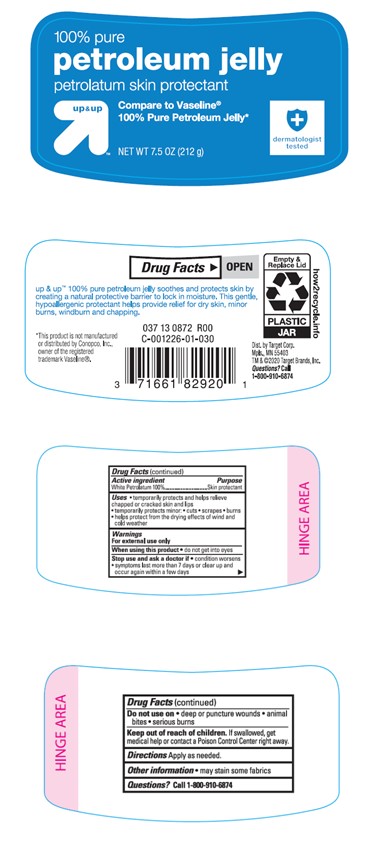 DRUG LABEL: Target Up and Up Petroleum Jelly
NDC: 11673-132 | Form: JELLY
Manufacturer: TARGET CORPORATION
Category: otc | Type: HUMAN OTC DRUG LABEL
Date: 20241014

ACTIVE INGREDIENTS: PETROLATUM 100 g/100 g

TARGET UP & UP PETROLEUM JELLY 100% PURE

Active ingredient

White Petrolatum 100%

Purpose

Skin protectant

Uses

- temporarily protects minor:

• cuts

• scrapes

• burns

- temporarily protects and helps relieve chapped or cracked skin and lips
- helps protect from the dying effects of wind and cold weather

Warnings

For external use only

When using this product

• do not get into eyes

Stop use and ask a doctor if

• condition worsens • symptoms last more than 7 days or clear up and occur again within a few days

Do not use on

• deep or puncture wounds • animal bites • serious burns

Keep out of reach of children.

If swallowed, get medical help or contact a Poison Control Center right away.

Directions

Apply as needed.

Other information

- may stain some fabrics

Inactive Ingredients

None

Label

TARGET UP & UP PETROLEUM JELLY 100% PURE

7.5 OZ (212g)

NDC 11673-022-59